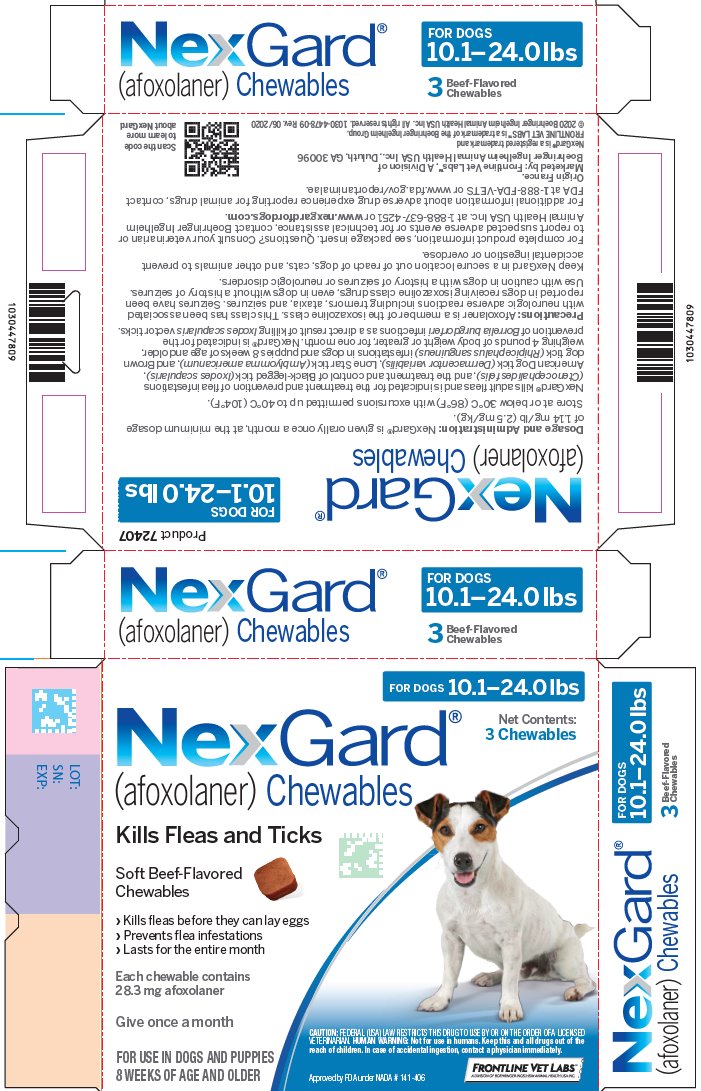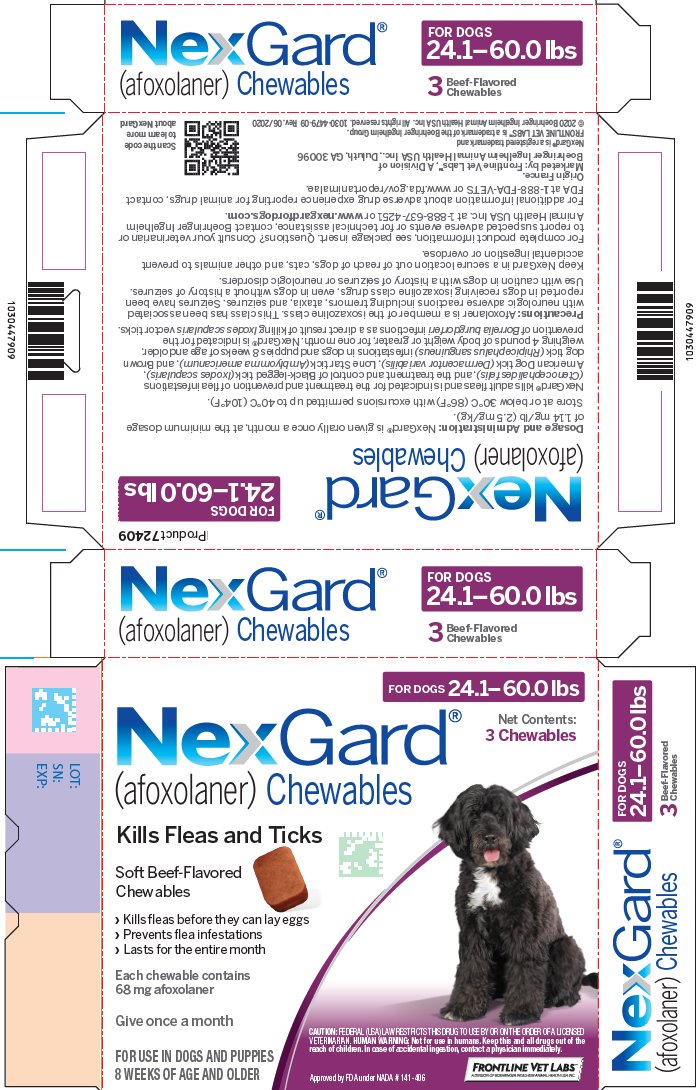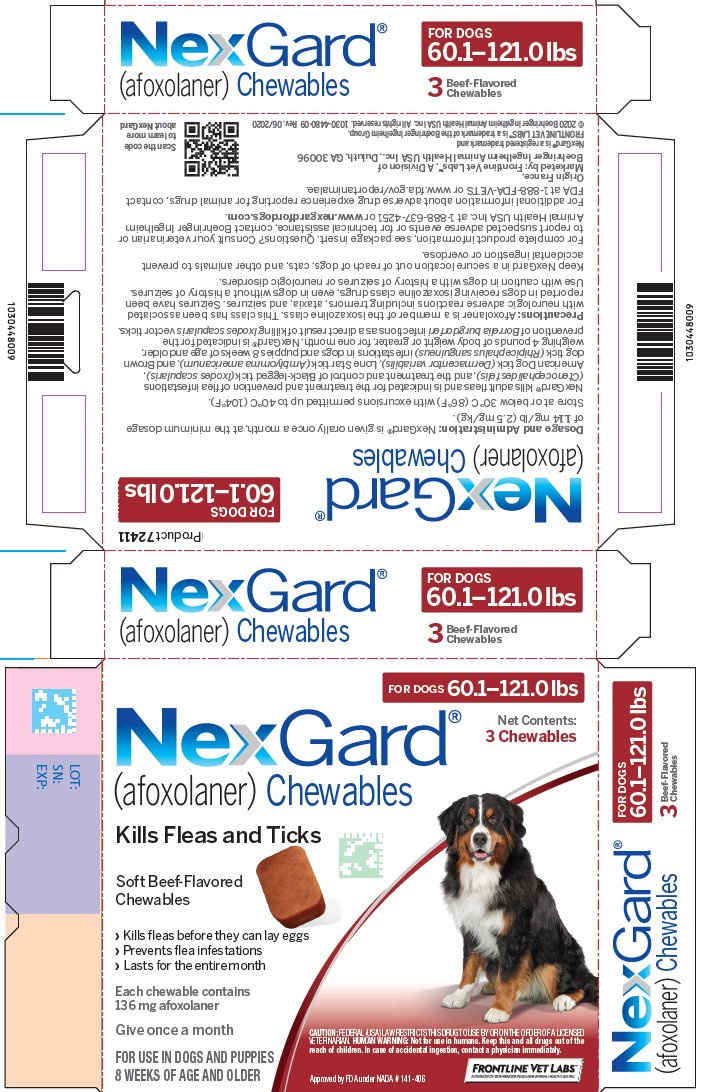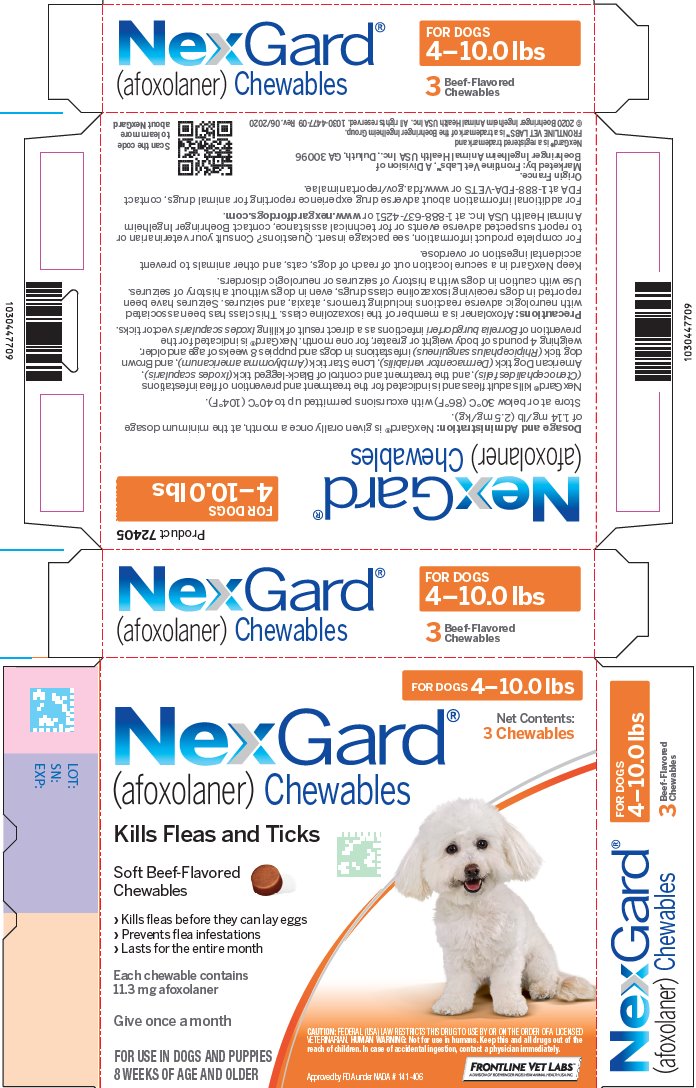 DRUG LABEL: NexGard
NDC: 59415-2405 | Form: TABLET, CHEWABLE
Manufacturer: Frontline Vet Labs
Category: animal | Type: PRESCRIPTION ANIMAL DRUG LABEL
Date: 20250925

ACTIVE INGREDIENTS: afoxolaner 11.3 mg/1 1

NexGard®
(afoxolaner) Chewables

CAUTION: Federal (USA) law restricts this drug to use by or on the order of a licensed veterinarian.

Description:

NexGard® (afoxolaner) is available in four sizes of beef-flavored, soft chewables for oral administration to dogs and puppies according to their weight. Each chewable is formulated to provide a minimum afoxolaner dosage of 1.14 mg/lb (2.5 mg/kg). Afoxolaner has the chemical composition 1-Naphthalenecarboxamide, 4-[5-[3-chloro-5-(trifluoromethyl)-phenyl]-4,5-dihydro-5-(trifluoromethyl)-3-isoxazolyl]-N-[2-oxo-2-[(2,2,2-trifluoroethyl)amino]ethyl.

Indications:

NexGard kills adult fleas and is indicated for the treatment and prevention of flea infestations (Ctenocephalides felis), and the treatment and control of Black-legged tick (Ixodes scapularis), American Dog tick (Dermacentor variabilis), Lone Star tick (Amblyomma americanum), and Brown dog tick (Rhipicephalus sanguineus) infestations in dogs and puppies 8 weeks of age and older, weighing 4 pounds of body weight or greater, for one month. NexGard is indicated for the prevention of Borrelia burgdorferi infections as a direct result of killing lxodes scapularis vector ticks.

Dosage and Administration:

NexGard is given orally once a month, at the minimum dosage of 1.14 mg/lb (2.5 mg/kg).

Dosing Schedule:

Body Weight | Afoxolaner Per Chewable (mg) | Chewables Administered
4.0 to 10.0 lbs. | 11.3 | One
10.1 to 24.0 lbs. | 28.3 | One
24.1 to 60.0 lbs. | 68 | One
60.1 to 121.0 lbs. | 136 | One
Over 121.0 lbs. | Administer the appropriate combination of chewables

NexGard can be administered with or without food. Care should be taken that the dog consumes the complete dose, and treated animals should be observed for a few minutes to ensure that part of the dose is not lost or refused. If it is suspected that any of the dose has been lost or if vomiting occurs within two hours of administration, redose with another full dose. If a dose is missed, administer NexGard and resume a monthly dosing schedule.

Flea Treatment and Prevention:

Treatment with NexGard may begin at any time of the year. In areas where fleas are common year-round, monthly treatment with NexGard should continue the entire year without interruption.

To minimize the likelihood of flea reinfestation, it is important to treat all animals within a household with an approved flea control product.

Tick Treatment and Control:

Treatment with NexGard may begin at any time of the year (see Effectiveness).

Contraindications:

There are no known contraindications for the use of NexGard.

Warnings:

Not for use in humans. Keep this and all drugs out of the reach of children. In case of accidental ingestion, contact a physician immediately.

Keep NexGard in a secure location out of reach of dogs, cats, and other animals to prevent accidental ingestion or overdose.

Precautions:

Afoxolaner is a member of the isoxazoline class. This class has been associated with neurologic adverse reactions including tremors, ataxia, and seizures. Seizures have been reported in dogs receiving isoxazoline class drugs, even in dogs without a history of seizures. Use with caution in dogs with a history of seizures or neurologic disorders.

The safe use of NexGard in breeding, pregnant or lactating dogs has not been evaluated.

Adverse Reactions:

In a well-controlled US field study, which included a total of 333 households and 615 treated dogs (415 administered afoxolaner; 200 administered active control), no serious adverse reactions were observed with NexGard.

Over the 90-day study period, all observations of potential adverse reactions were recorded. The most frequent reactions reported at an incidence of > 1% within any of the three months of observations are presented in the following table. The most frequently reported adverse reaction was vomiting. The occurrence of vomiting was generally self-limiting and of short duration and tended to decrease with subsequent doses in both groups. Five treated dogs experienced anorexia during the study, and two of those dogs experienced anorexia with the first dose but not subsequent doses.

Table 1: Dogs With Adverse Reactions.
 | Treatment Group
 | Afoxolaner |  | Oral active control
 | N [Number of dogs in the afoxolaner treatment group with the identified abnormality.] | % (n=415) | N [Number of dogs in the control group with the identified abnormality.] | % (n=200)
Vomiting (with and without blood) | 17 | 4.1 | 25 | 12.5
Dry/Flaky Skin | 13 | 3.1 | 2 | 1.0
Diarrhea (with and without blood) | 13 | 3.1 | 7 | 3.5
Lethargy | 7 | 1.7 | 4 | 2.0
Anorexia | 5 | 1.2 | 9 | 4.5

In the US field study, one dog with a history of seizures experienced a seizure on the same day after receiving the first dose and on the same day after receiving the second dose of NexGard. This dog experienced a third seizure one week after receiving the third dose. The dog remained enrolled and completed the study. Another dog with a history of seizures had a seizure 19 days after the third dose of NexGard. The dog remained enrolled and completed the study. A third dog with a history of seizures received NexGard and experienced no seizures throughout the study.

Post-Approval Experience (July 2018):

The following adverse events are based on post-approval adverse drug experience reporting. Not all adverse events are reported to FDA/CVM. It is not always possible to reliably estimate the adverse event frequency or establish a causal relationship to product exposure using these data.

The following adverse events reported for dogs are listed in decreasing order of reporting frequency for NexGard:

Vomiting, pruritus, lethargy, diarrhea (with and without blood), anorexia, seizure, hyperactivity/restlessness, panting, erythema, ataxia, dermatitis (including rash, papules), allergic reactions (including hives, swelling) and tremors.

Contact Information:

For a copy of the Safety Data Sheet (SDS) or to report suspected adverse drug events, contact Boehringer Ingelheim Animal Health USA Inc. at 1-888-637-4251 or www.nexgardfordogs.com.

For additional information about adverse drug experience reporting for animal drugs, contact FDA at 1-888-FDA-VETS or www.fda.gov/reportanimalae.

Mode of Action:

Afoxolaner is a member of the isoxazoline family, shown to bind at a binding site to inhibit insect and acarine ligand-gated chloride channels, in particular those gated by the neurotransmitter gamma-aminobutyric acid (GABA), thereby blocking pre- and post-synaptic transfer of chloride ions across cell membranes. Prolonged afoxolaner-induced hyperexcitation results in uncontrolled activity of the central nervous system and death of insects and acarines. The selective toxicity of afoxolaner between insects and acarines and mammals may be inferred by the differential sensitivity of the insects and acarines' GABA receptors versus mammalian GABA receptors.

Effectiveness:

In a well-controlled laboratory study, NexGard began to kill fleas four hours after initial administration and demonstrated >99% effectiveness at eight hours. In a separate well-controlled laboratory study, NexGard demonstrated 100% effectiveness against adult fleas 24 hours post-infestation for 35 days, and was ≥93% effective at 12 hours post-infestation through Day 21, and on Day 35. On Day 28, NexGard was 81.1% effective 12 hours post-infestation. Dogs in both the treated and control groups that were infested with fleas on Day -1 generated flea eggs at 12- and 24-hours post-treatment (0-11 eggs and 1-17 eggs in the NexGard treated dogs, and 4-90 eggs and 0-118 eggs in the control dogs, at 12- and 24-hours, respectively). At subsequent evaluations post-infestation, fleas from dogs in the treated group were essentially unable to produce any eggs (0-1 eggs) while fleas from dogs in the control group continued to produce eggs (1-141 eggs).

In a 90-day US field study conducted in households with existing flea infestations of varying severity, the effectiveness of NexGard against fleas on the Day 30, 60 and 90 visits compared with baseline was 98.0%, 99.7%, and 99.9%, respectively.

Collectively, the data from the three studies (two laboratory and one field) demonstrate that NexGard kills fleas before they can lay eggs, thus preventing subsequent flea infestations after the start of treatment of existing flea infestations.

In well-controlled laboratory studies, NexGard demonstrated >97% effectiveness against Dermacentor variabilis, >94% effectiveness against Ixodes scapularis, and >93% effectiveness against Rhipicephalus sanguineus, 48 hours post-infestation for 30 days. At 72 hours post-infestation, NexGard demonstrated >97% effectiveness against Amblyomma americanum for 30 days. In two separate, well-controlled laboratory studies, NexGard was effective at preventing Borrelia burgdorferi infections after dogs were infested with lxodes scapularis vector ticks 28 days post-treatment.

Animal Safety:

In a margin of safety study, NexGard was administered orally to 8 to 9-week-old Beagle puppies at 1, 3, and 5 times the maximum exposure dose (6.3 mg/kg) for three treatments every 28 days, followed by three treatments every 14 days, for a total of six treatments. Dogs in the control group were sham-dosed. There were no clinically-relevant effects related to treatment on physical examination, body weight, food consumption, clinical pathology (hematology, clinical chemistries, or coagulation tests), gross pathology, histopathology or organ weights. Vomiting occurred throughout the study, with a similar incidence in the treated and control groups, including one dog in the 5× group that vomited four hours after treatment.

In a well-controlled field study, NexGard was used concomitantly with other medications, such as vaccines, anthelmintics, antibiotics (including topicals), steroids, NSAIDS, anesthetics, and antihistamines. No adverse reactions were observed from the concomitant use of NexGard with other medications.

Storage Information:

Store at or below 30°C (86°F) with excursions permitted up to 40°C (104°F).

How Supplied:

NexGard is available in four sizes of beef-flavored soft chewables: 11.3, 28.3, 68 or 136 mg afoxolaner. Each chewable size is available in color-coded packages of 1, 3 or 6 beef-flavored chewables.

Approved by FDA under NADA # 141-406

Marketed by:
Frontline Vet Labs™, a Division of Boehringer Ingelheim Animal Health USA Inc.
Duluth, GA 30096

NexGard® is a registered trademark and
FRONTLINE VET LABS™ is a trademark of the Boehringer Ingelheim Group.
©2020 Boehringer Ingelheim Animal Health USA Inc. All rights reserved.

1050-4493-10
Rev. 06/2020

PRINCIPAL DISPLAY PANEL - 11.3 mg Tablet Carton

FOR DOGS 4–10.0 lbs

NexGard®
(afoxolaner) Chewables

Net Contents:
3 Chewables

Kills Fleas and Ticks

Soft Beef-Flavored
Chewables

> Kills fleas before they can lay eggs
> Prevents flea infestations
> Lasts for the entire month

Each chewable contains
11.3 mg afoxolaner

Give once a month

FOR USE IN DOGS AND PUPPIES
8 WEEKS OF AGE AND OLDER

APPROVED BY FDA UNDER NADA # 141-406

CAUTION: FEDERAL (USA) LAW RESTRICTS THIS DRUG TO USE BY OR ON THE ORDER OF A LICENSED VETERINARIAN. HUMAN WARNING: Not for use in humans. Keep this and all drugs out of thereach of children. In case of accidental ingestion, contact a physician immediately.

PRINCIPAL DISPLAY PANEL - 28.3 mg Tablet Carton

FOR DOGS 10.1–24.0 lbs

NexGard®
(afoxolaner) Chewables

Net Contents:
3 Chewables

Kills Fleas and Ticks

Soft Beef-Flavored
Chewables

> Kills fleas before they can lay eggs
> Prevents flea infestations
> Lasts for the entire month

Each chewable contains
28.3 mg afoxolaner

Give once a month

FOR USE IN DOGS AND PUPPIES
8 WEEKS OF AGE AND OLDER

APPROVED BY FDA UNDER NADA # 141-406

CAUTION: FEDERAL (USA) LAW RESTRICTS THIS DRUG TO USE BY OR ON THE ORDER OF A LICENSED VETERINARIAN. HUMAN WARNING: Not for use in humans. Keep this and all drugs out of thereach of children. In case of accidental ingestion, contact a physician immediately.

PRINCIPAL DISPLAY PANEL - 68 mg Tablet Carton

FOR DOGS 24.1–60.0 lbs

NexGard®
(afoxolaner) Chewables

Net Contents:
3 Chewables

Kills Fleas and Ticks

Soft Beef-Flavored
Chewables

> Kills fleas before they can lay eggs
> Prevents flea infestations
> Lasts for the entire month

Each chewable contains
68 mg afoxolaner

Give once a month

FOR USE IN DOGS AND PUPPIES
8 WEEKS OF AGE AND OLDER

APPROVED BY FDA UNDER NADA # 141-406

CAUTION: FEDERAL (USA) LAW RESTRICTS THIS DRUG TO USE BY OR ON THE ORDER OF A LICENSED VETERINARIAN. HUMAN WARNING: Not for use in humans. Keep this and all drugs out of thereach of children. In case of accidental ingestion, contact a physician immediately.

PRINCIPAL DISPLAY PANEL - 136 mg Tablet Carton

FOR DOGS 60.1–121.0 lbs

NexGard®
(afoxolaner) Chewables

Net Contents:
3 Chewables

Kills Fleas and Ticks

Soft Beef-Flavored
Chewables

> Kills fleas before they can lay eggs
> Prevents flea infestations
> Lasts for the entire month

Each chewable contains
136 mg afoxolaner

Give once a month

FOR USE IN DOGS AND PUPPIES
8 WEEKS OF AGE AND OLDER

APPROVED BY FDA UNDER NADA # 141-406

CAUTION: FEDERAL (USA) LAW RESTRICTS THIS DRUG TO USE BY OR ON THE ORDER OF A LICENSED VETERINARIAN. HUMAN WARNING: Not for use in humans. Keep this and all drugs out of thereach of children. In case of accidental ingestion, contact a physician immediately.